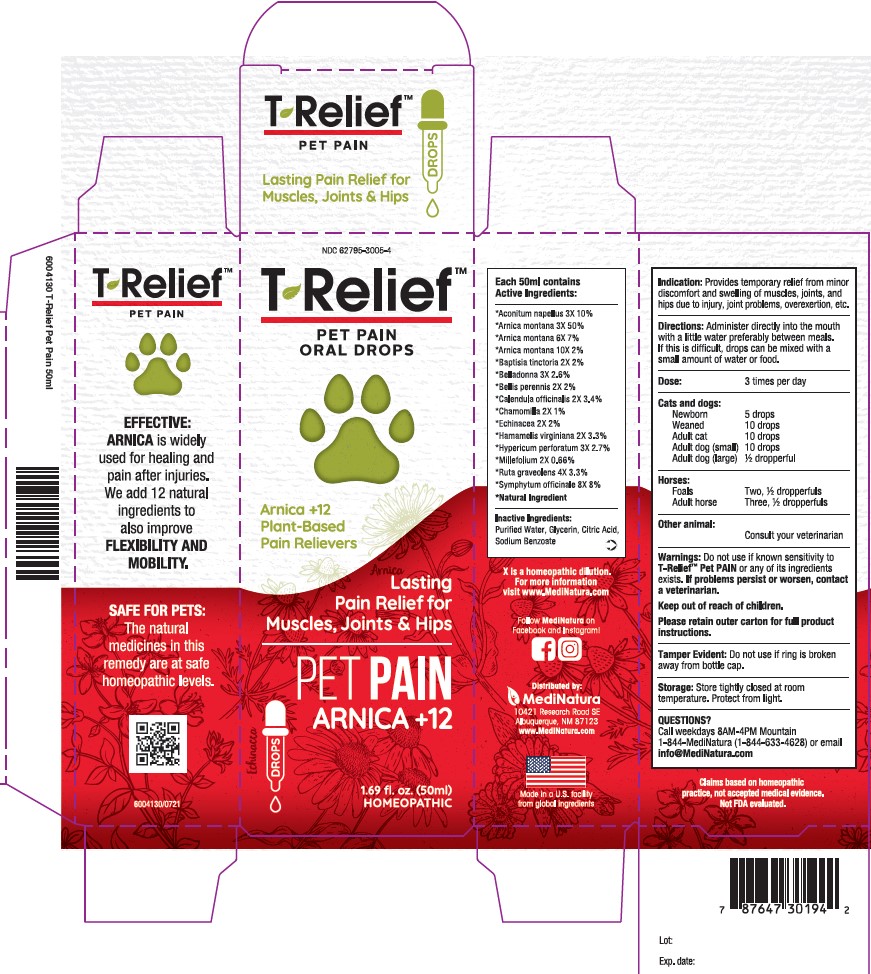 DRUG LABEL: T-Relief Pet Pain
NDC: 62795-3005 | Form: SOLUTION/ DROPS
Manufacturer: MediNatura New Mexico Inc
Category: homeopathic | Type: OTC ANIMAL DRUG LABEL
Date: 20230918

ACTIVE INGREDIENTS: ARNICA MONTANA 3 [hp_X]/50 mL; CALENDULA OFFICINALIS FLOWERING TOP 2 [hp_X]/50 mL; HAMAMELIS VIRGINIANA ROOT BARK/STEM BARK 2 [hp_X]/50 mL; BAPTISIA TINCTORIA ROOT 2 [hp_X]/50 mL; BELLIS PERENNIS 2 [hp_X]/50 mL; ECHINACEA ANGUSTIFOLIA 2 [hp_X]/50 mL; ACONITUM NAPELLUS 3 [hp_X]/50 mL; MATRICARIA CHAMOMILLA 2 [hp_X]/50 mL; ACHILLEA MILLEFOLIUM 2 [hp_X]/50 mL; ATROPA BELLADONNA 3 [hp_X]/50 mL; HYPERICUM PERFORATUM 3 [hp_X]/50 mL; RUTA GRAVEOLENS FLOWERING TOP 4 [hp_X]/50 mL; COMFREY ROOT 8 [hp_X]/50 mL
INACTIVE INGREDIENTS: WATER; GLYCERIN; CITRIC ACID ACETATE; Sodium Benzoate

T-Relief Pet Pain

Warnings

Warnings: Do not use if known sensitivity to T-Relief™ Pet PAIN or any of
its ingredients exists. If problems persist or worsen, contact a veterinarian.
Keep out of reach of children.

Indication:

Provides temporary relief from minor discomfort and swelling
of muscles, joints, and hips due to injury, joint problems, overexertion, etc

Directions

Directions: Administer directly into the mouth with a little water preferably
between meals. If this is difficult, drops can be mixed with a small amount
of water or food.–
Dose: 3 times per day – Cats & dogs: Newborn – 5 drops. Weaned – 10
drops. Adult cat – 10 drops. Adult dog (small) – 10 drops. Adult dog (large)
– ½ dropperful. Horses: Foals – Two, ½ dropperfuls. Adult horse – Three,
½ dropperfuls. Other animal: Consult your veterinarian.–

Inactives

Purified Water, Glycerin, Citric Acid, Sodium Benzoate

Keep out of reach of children.

Purpose

Provides temporary relief from minor discomfort and swelling
of muscles, joints, and hips due to injury, joint problems, overexertion, etc

Active Ingredients

Each 50mL contains: *Aconitum napellus 3X 10%,
*Arnica montana 3X 50%, *Arnica montana 6X 7%, *Arnica montana
10X 2%, *Baptisia tinctoria 2X 2%, *Belladonna 3X 2.6%, *Bellis
perennis 2X 2%, *Calendula officinalis 2X 3.4%, *Chamomilla 2X 1%,
*Echinacea 2X 2%, *Hamamelis virginiana 2X 3.3%, *Hypericum
perforatum 3X 2.7%, *Millefolium 2X